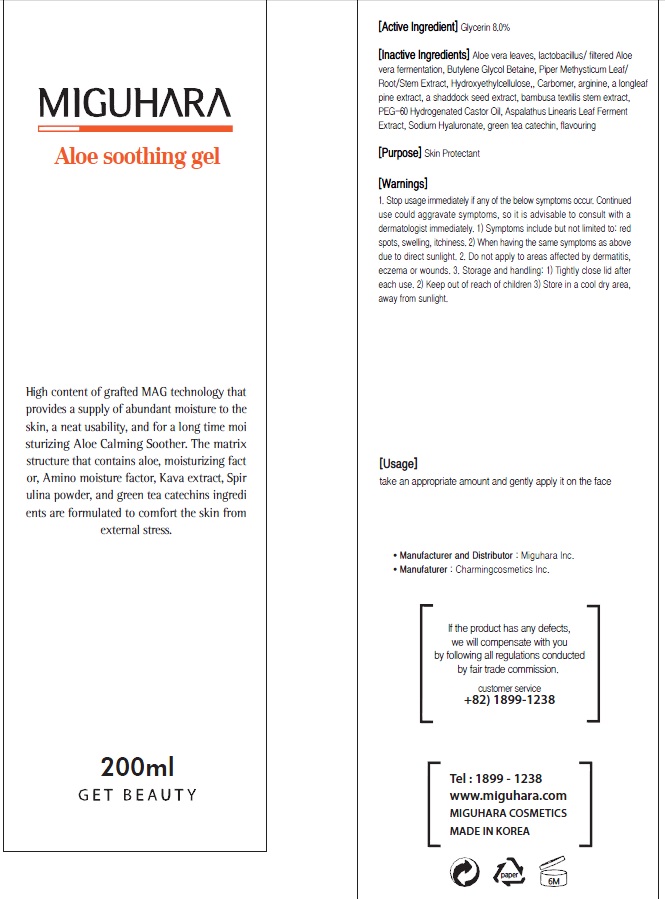 DRUG LABEL: Aloe Soothing
NDC: 70380-080 | Form: GEL
Manufacturer: MIGUHARA
Category: otc | Type: HUMAN OTC DRUG LABEL
Date: 20160218

ACTIVE INGREDIENTS: Glycerin 16.0 g/200 mL
INACTIVE INGREDIENTS: ALOE VERA LEAF; Butylene Glycol

ACTIVE INGREDIENT

Active Ingredient: Glycerin 8.0%

INACTIVE INGREDIENT

Inactive Ingredients: Aloe vera leaves, lactobacillus/ filtered Aloe vera fermentation, Butylene Glycol, Betaine, Piper Methysticum Leaf/Root/Stem Extract, Hydroxyethylcellulose, Carbomer, arginine, a longleaf pine extract, a shaddock seed extract, bambusa textilis stem extract, PEG-60 Hydrogenated Castor Oil, Aspalathus Linearis Leaf Ferment Extract, Sodium Hyaluronate, green tea catechin, flavouring.

PURPOSE

Purpose: Skin Protectant

WARNINGS

1. Stop usage immediately if any of the below symptoms occur. Continued use could aggravate symptoms, so it is advisable to consult with a dermatologist immediately. 1) Symptoms include but not limited to: red spots, swelling, itchiness. 2) When having the same symptoms as above due to direct sunlight. 2. Do not apply to areas affected by dermatitis, eczema or wounds. 3. Storage and handling: 1) Tightly close lid after each use. 2 Keep out of reach of children 3) Store in a cool dry area, away from sunlight

KEEP OUT OF REACH OF CHILDREN

Usage

Usage: Take an appropriate amount and gently apply it on the face.

Usage

Usage: Take an appropriate amount and gently apply it on the face.